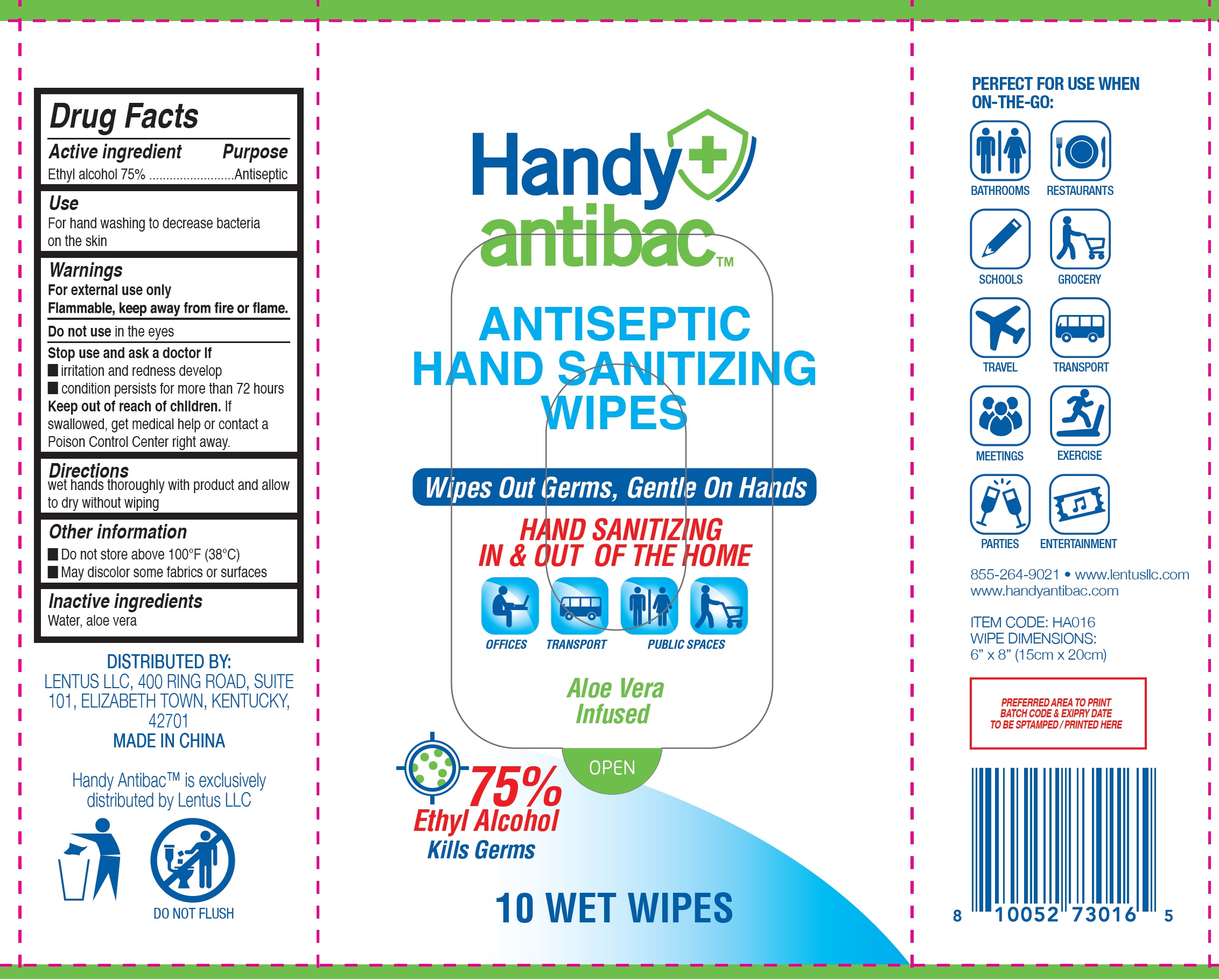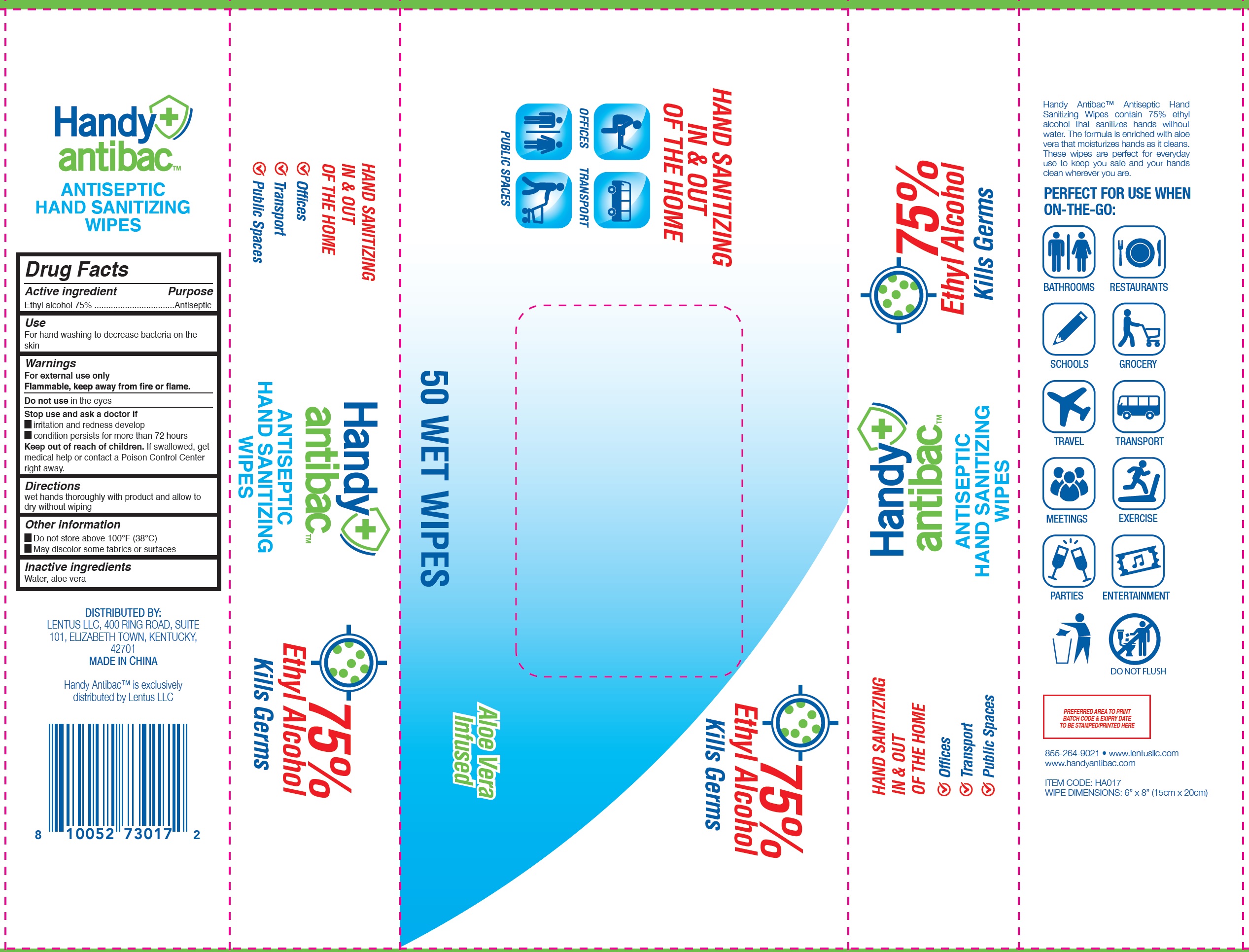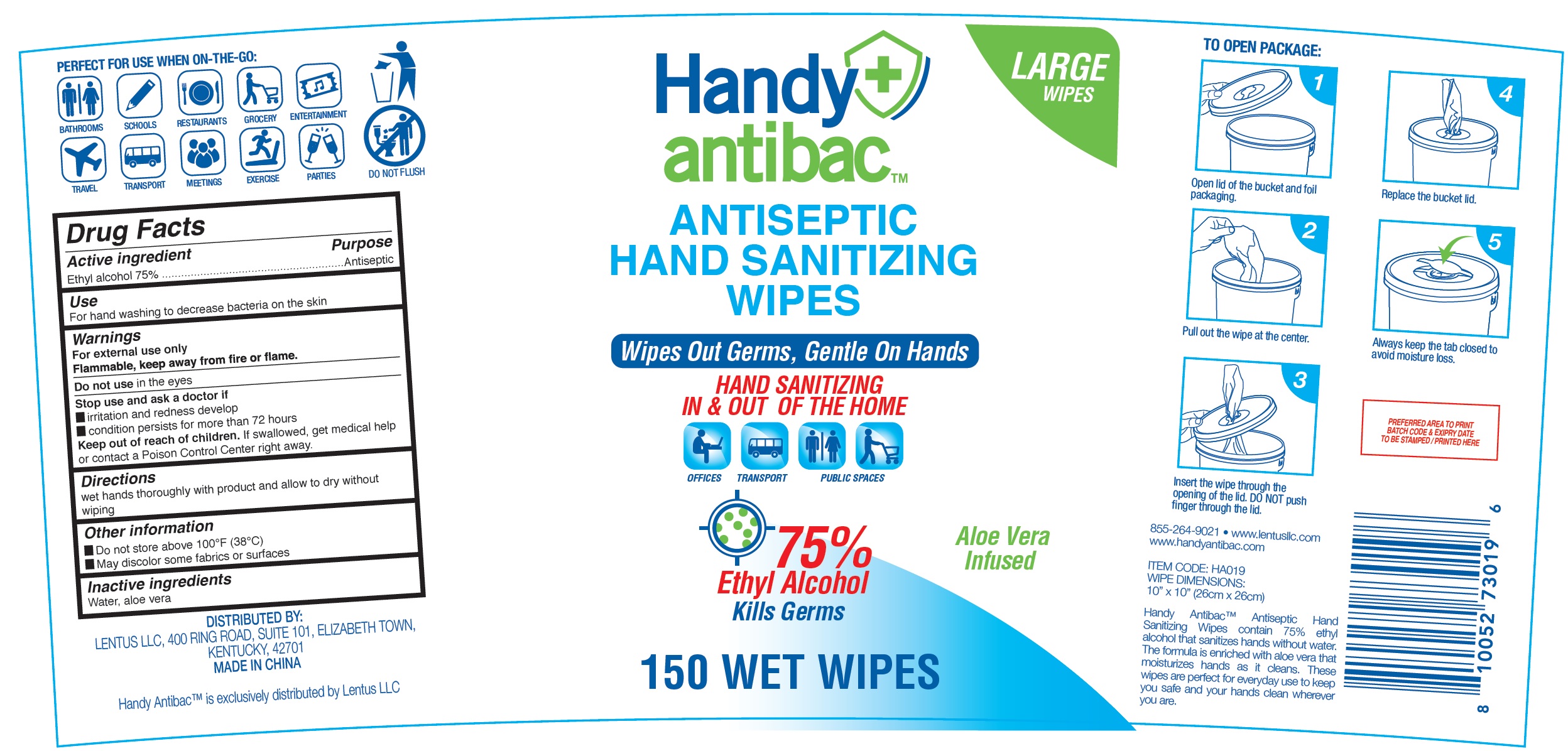 DRUG LABEL: Handy Antibac Antiseptic Hand Sanitizing Wipes
NDC: 79873-001 | Form: CLOTH
Manufacturer: Lentus LLC
Category: otc | Type: HUMAN OTC DRUG LABEL
Date: 20200806

ACTIVE INGREDIENTS: ALCOHOL 0.75 mL/1 mL
INACTIVE INGREDIENTS: WATER; ALOE VERA LEAF

Handy Antibac Antiseptic Hand Sanitizing Wipes

Active ingredient

Ethyl alcohol 75%

Purpose

Antiseptic

Use

For hand washing to decrease bacteria on the skin

Warnings

For external use only Flammable, keep away from fire or flame.

Do not use

in the eyes.

Stop use and ask a doctor if

- irritation and redness develop
- condition persists for more than 72 hours

Keep out of reach of children.

If swallowed, get medical help or contact a Poison Control Center right away.

Directions

wet hands thoroughly with product and allow to dry without wiping

Other information

- Do not store above 100°F (38°C)
- May discolor some fabrics or surfaces

Inactive ingredients

Water, aloe vera